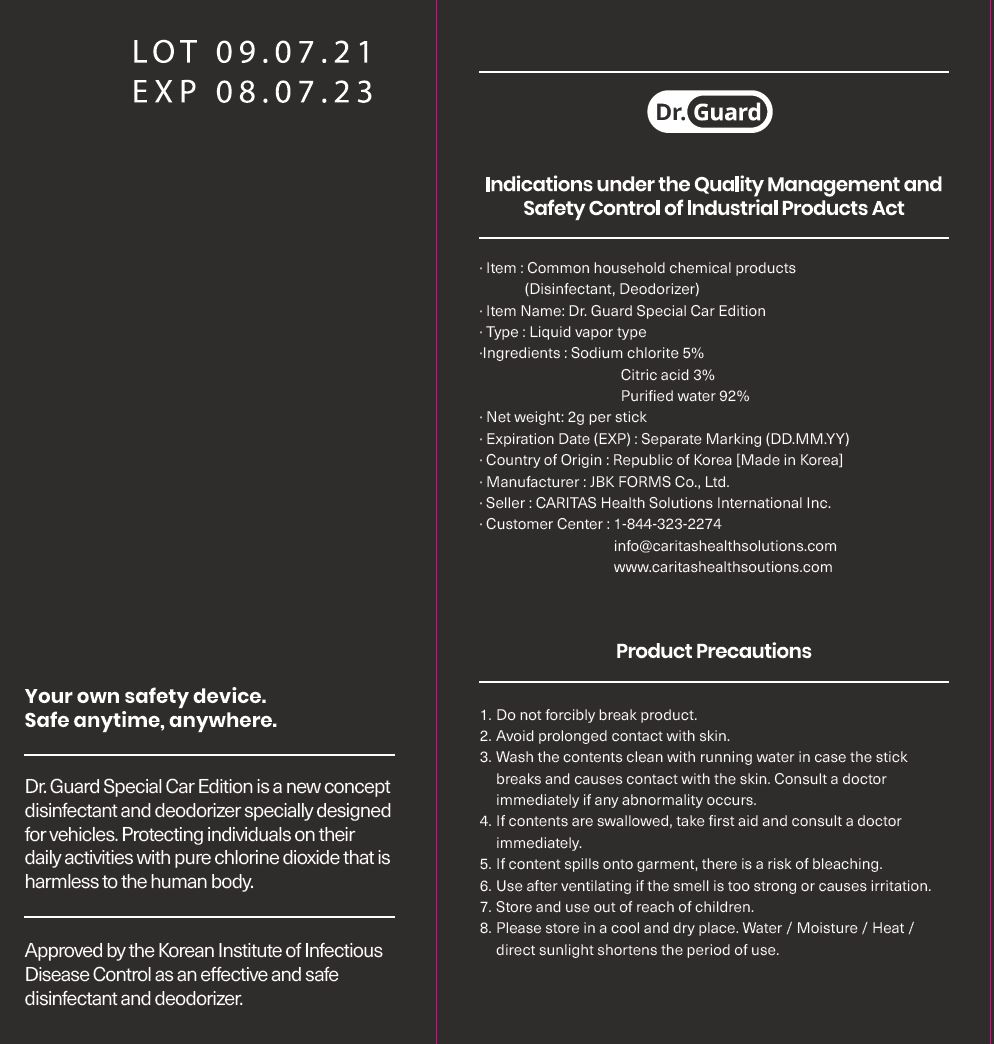 DRUG LABEL: Dr. Guard Special Car Edition
NDC: 82358-0003 | Form: LIQUID
Manufacturer: JBK FORMS Co Ltd
Category: otc | Type: HUMAN OTC DRUG LABEL
Date: 20211104

ACTIVE INGREDIENTS: SODIUM CHLORITE 5 g/100 g
INACTIVE INGREDIENTS: CITRIC ACID MONOHYDRATE; WATER

Drug Facts

ACTIVE INGREDIENT

sodium chlorite

INACTIVE INGREDIENT

citric acid, water

PURPOSE

Disinfectant · Deodorizer

KEEP OUT OF REACH OF THE CHILDREN

INDICATIONS AND USAGE

apply where needed

WARNINGS

■ For external use only.

■ Do not use in eyes.

■ lf swallowed, get medical help promptly.

■ Stop use, ask doctor lf irritation occurs.

■ Keep out of reach of children.

DOSAGE AND ADMINISTRATION

for external use only